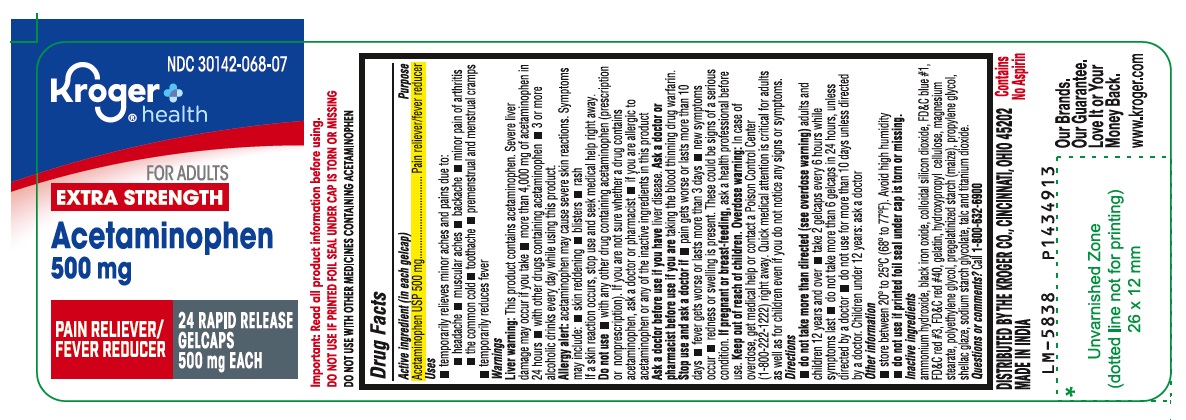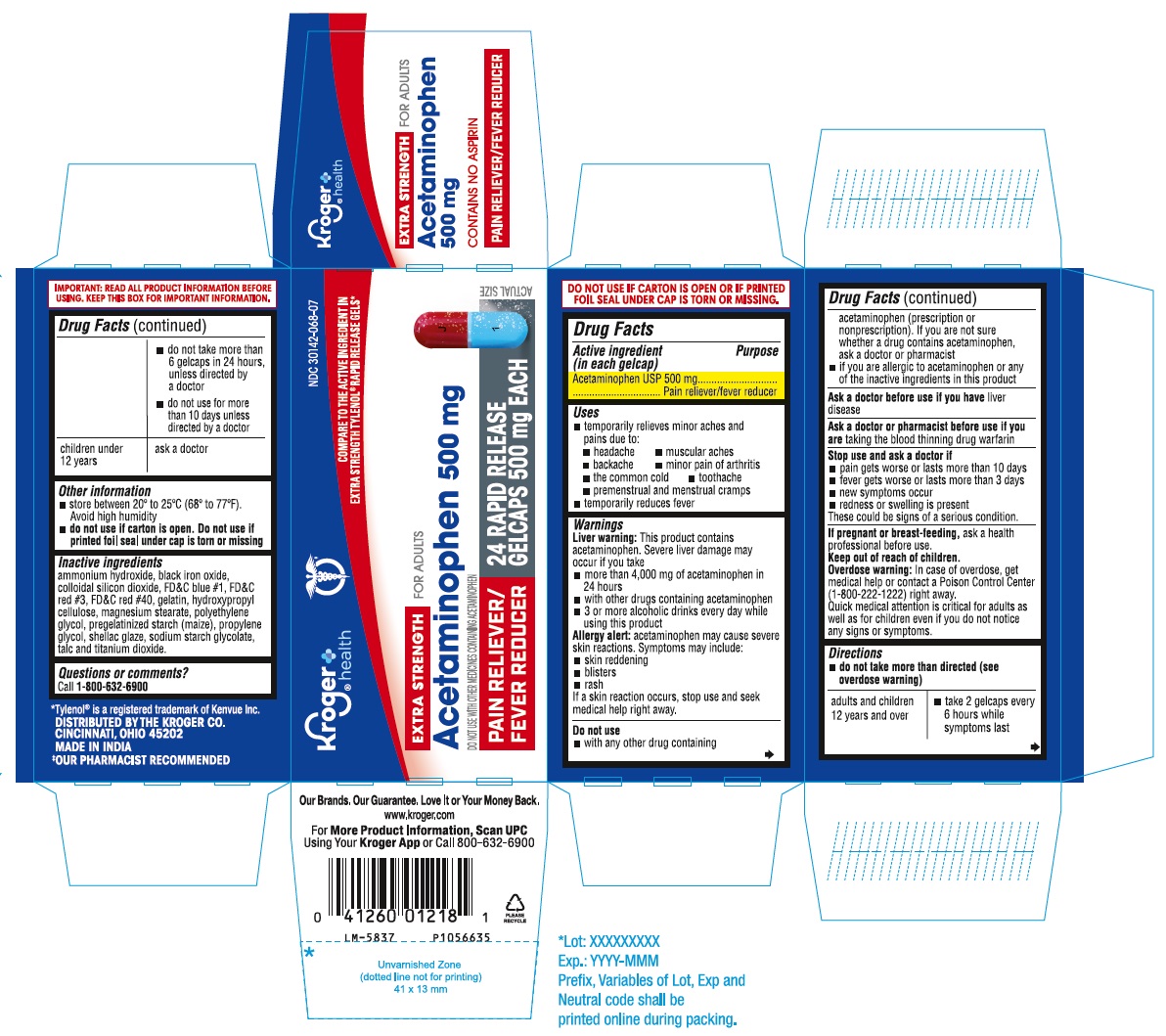 DRUG LABEL: Acetaminophen Extra Strength
NDC: 30142-068 | Form: TABLET
Manufacturer: KROGER COMPANY
Category: otc | Type: Human OTC Drug Label
Date: 20241022

ACTIVE INGREDIENTS: ACETAMINOPHEN 500 mg/1 1
INACTIVE INGREDIENTS: AMMONIA; FERROSOFERRIC OXIDE; SILICON DIOXIDE; FD&C BLUE NO. 1; FD&C RED NO. 3; FD&C RED NO. 40; GELATIN, UNSPECIFIED; HYDROXYPROPYL CELLULOSE, UNSPECIFIED; MAGNESIUM STEARATE; POLYETHYLENE GLYCOL, UNSPECIFIED; STARCH, CORN; PROPYLENE GLYCOL; SHELLAC; SODIUM STARCH GLYCOLATE TYPE A POTATO; TALC; TITANIUM DIOXIDE

Drug Facts

Active ingredient (in each gelcap)
Acetaminophen USP 500 mg

Purpose

Pain reliever/fever reducer

Uses

- temporarily relieves minor aches and pains due to:
  - headache
  - muscular aches
  - backache
  - minor pain of arthritis
  - the common cold
  - toothache
  - premenstrual and menstrual cramps
- temporarily reduces fever

Warnings

Liver warning: This product contains acetaminophen. Severe liver damage may occur if you take

- more than 4,000 mg of acetaminophen in 24 hours
- with other drugs containing acetaminophen
- 3 or more alcoholic drinks every day while using this product

Allergy alert: acetaminophen may cause severe skin reactions.

Symptoms may include:

- skin reddening
- blisters
- rash

If a skin reaction occurs, stop use and seek medical help right away.

Do not use

- with any other drug containing acetaminophen (prescription or nonprescription). If you are not sure whether a drug contains acetaminophen, ask a doctor or pharmacist.
- if you are allergic to acetaminophen or any of the inactive ingredients in this product

Ask a doctor before use if you have

liver disease

Ask a doctor or pharmacist before use if you are

taking the blood thinning drug warfarin

Stop use and ask a doctor if

- pain gets worse or lasts more than 10 days
- fever gets worse or lasts more than 3 days
- new symptoms occur
- redness or swelling is present

These could be signs of a serious condition.

If pregnant or breast-feeding,

ask a health professional before use.

Keep out of reach of children.

Overdose warning: In case of overdose, get medical help or contact a Poison Control Center (1-800-222-1222) right away.
Quick medical attention is critical for adults as well as for children even if you do not notice any signs or symptoms.

Directions

- do not take more than directed (see overdose warning)

adults and children 12 years and over | - take 2 gelcaps every 6 hours while symptoms last - do not take more than 6 gelcaps in 24 hours, unless directed by a doctor - do not use for more than 10 days unless directed by a doctor
children under 12 years | ask a doctor

Other information

- store between 20° to 25°C (68° to 77°F). Avoid high humidity
- do not use if carton is open. Do not use if printed foil seal under cap is torn or missing

Inactive ingredients

ammonium hydroxide, black iron oxide, colloidal silicon dioxide, FD&C blue #1, FD&C red #3, FD&C red #40, gelatin, hydroxypropyl cellulose, magnesium stearate, polyethylene glycol, pregelatinized starch (maize), propylene glycol, shellac glaze, sodium starch glycolate, talc and titanium dioxide.

Questions or comments?

call 1-800-632-6900
DISTRIBUTED BY THE KROGER CO.
CINCINNATI, OHIO 45202
MADE IN INDIA

PACKAGE LABEL-PRINCIPAL DISPLAY PANEL 500 mg (24 Gelcaps Container Label)

NDC 30142-068-07
Kroger®
health
FOR ADULTS
EXTRA STRENGTH
Acetaminophen
500 mg
PAIN RELIEVER/
FEVER REDUCER
24 RAPID RELEASE
GELCAPS
500 mg EACH

PACKAGE LABEL-PRINCIPAL DISPLAY PANEL 500 mg (24 Gelcaps Container Carton Label)

NDC 30142-068-07
Kroger®
health
COMPARE TO THE ACTIVE INGREDIENT IN
EXTRA STRENGTH TYLENOL® RAPID RELEASE GELS*
EXTRA STRENGTH FOR ADULTS
Acetaminophen 500 mg
DO NOT USE WITH OTHER MEDICINES CONTAINING ACETAMINOPHEN
PAIN RELIEVER/
FEVER REDUCER
24 RAPID RELEASE
GELCAPS 500 mg EACH ACTUAL SIZE